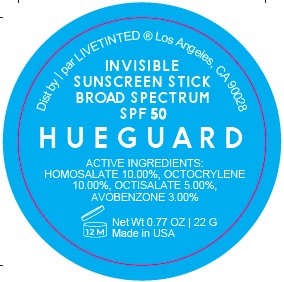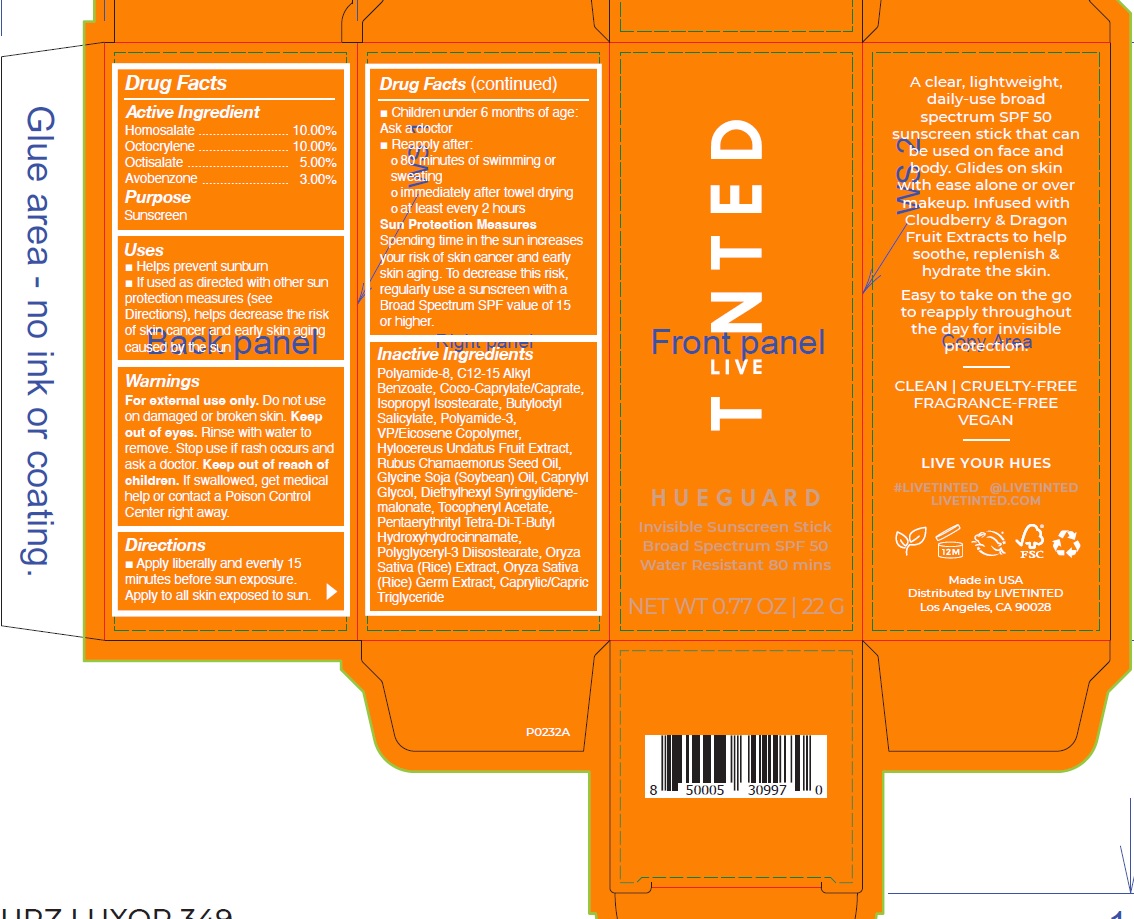 DRUG LABEL: LIVE TINTED Hueguard Invisible Sunscreen Stick Broad Spectrum SPF 50 Water Resistant 80 Mins
NDC: 82153-276 | Form: STICK
Manufacturer: Live Tinted, Inc.
Category: otc | Type: HUMAN OTC DRUG LABEL
Date: 20231028

ACTIVE INGREDIENTS: HOMOSALATE 100 mg/1 g; OCTOCRYLENE 100 mg/1 g; OCTISALATE 50 mg/1 g; AVOBENZONE 30 mg/1 g
INACTIVE INGREDIENTS: ALKYL (C12-15) BENZOATE; COCO-CAPRYLATE/CAPRATE; ISOPROPYL ISOSTEARATE; BUTYLOCTYL SALICYLATE; SELENICEREUS UNDATUS FRUIT; RUBUS CHAMAEMORUS SEED OIL; SOYBEAN OIL; CAPRYLYL GLYCOL; DIETHYLHEXYL SYRINGYLIDENEMALONATE; .ALPHA.-TOCOPHEROL ACETATE; PENTAERYTHRITOL TETRAKIS(3-(3,5-DI-TERT-BUTYL-4-HYDROXYPHENYL)PROPIONATE); POLYGLYCERYL-3 DIISOSTEARATE; RICE GERM; WHITE RICE; MEDIUM-CHAIN TRIGLYCERIDES

LIVE TINTED. Hueguard Invisible Sunscreen Stick Broad Spectrum SPF 50 Water Resistant 80 Mins

Active Ingredient

Homosalate 10.00% Octocrylene 10.00% Octisalate 5.00% Avobenzone 3.00%

Purpose

Sunscreen

Uses

- Helps prevent sunburn
- If used as directed with other sun protection measures (see Directions), helps decrease the risk of skin cancer and early skin aging caused by the sun

Warnings

For external use only.

Do not use

on damaged or broken skin. Keep out of eyes. Rinse with water to remove.

Stop use

if rash occurs and ask a doctor.

Keep out of reach of children.

If swallowed, get medical help or contact a Poison Control Center right away.

Directions

- Apply liberally and evenly 15 minutes before sun exposure. Apply to all skin exposed to sun.
- Children under 6 months of age: Ask a doctor
- Reapply after:
- 80 minutes of swimming or sweating
- immediately after towel drying
- at least every 2 hours

Spending time in the sun increases your risk of skin cancer and early skin aging. To decrease this risk, regularly use a sunscreen with a Broad Spectrum SPF value of 15 or higher. Sun Protection Measures

Inactive Ingredients

Polyamide-8, C12-15 Alkyl Benzoate, Coco-Caprylate/Caprate, Isopropyl Isostearate, Butyloctyl Salicylate, Polyamide-3, VP/Eicosene Copolymer, Hylocereus Undatus Fruit Extract, Rubus Chamaemorus Seed Oil, Glycine Soja (Soybean) Oil, Caprylyl Glycol, Diethylhexyl Syringylidenemalonate, Tocopheryl Acetate, Pentaerythrityl Tetra-Di-T-Butyl Hydroxyhydrocinnamate, Polyglyceryl-3 Diisostearate, Oryza Sativa (Rice) Extract, Oryza Sativa (Rice) Germ Extract, Caprylic/Capric Triglyceride